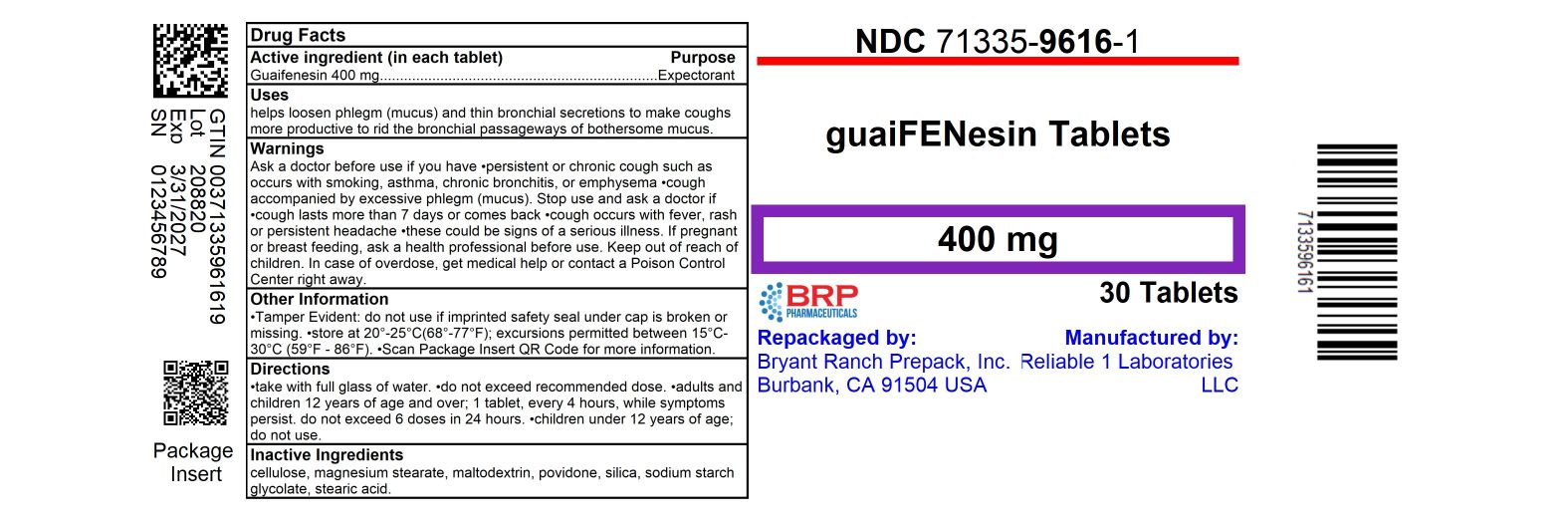 DRUG LABEL: Guaifenesin
NDC: 71335-9616 | Form: TABLET
Manufacturer: Bryant Ranch Prepack
Category: otc | Type: HUMAN OTC DRUG LABEL
Date: 20250331

ACTIVE INGREDIENTS: GUAIFENESIN 400 mg/1 1
INACTIVE INGREDIENTS: MICROCRYSTALLINE CELLULOSE; POVIDONE, UNSPECIFIED; MAGNESIUM STEARATE; MALTODEXTRIN

Guifenisen 400 mg

Active ingredient (in each caplet)

Guaifenesin 400 mg

Purpose

Expectorant

Uses

helps lossen phlegm (mucus) and thin bronchial secretions to rid the bronchial passageways of bothersone mucus and make coughs more productive

Warnings

Ask a doctor before use if you have

- persistent or chronic cough such as occurs with smoking, asthma, chronic bronchitis, or emphysema
- cough accompanied by too much phlegm (mucus)

Stop use and ask a doctor if cough lasts more then 7 days, comes back, or is accompanied by fever, rash, or persistent headache. These could be signes of serious illness.

Stop use and ask a doctor if cough lasts more than 7 days, comes back, or is accompanied by fever, rash, or persistent headache. these could be signs of a serious illness.

PREGNANCY OR BREAST FEEDING

If pregnant or breast-feeding, ask a health professional before use.

Keep out of reach of children. In case of overdose, get medical help or contact a Poison Control Center right away.

Directions

- do not take more than 6 doses in any 24- hour period
- this product is not intended for use in children under 12 years of age
- adults & children 12 years and over: 1 caplet every 4 hours
- children under 12 years: do not use

Other information

store at 15°-30°C (59°-86°F)

Inactive ingredients

colloidal silicon dioxide, magnesium stearate, maltodextrin, microsrystalline cellulose, providone, stearic acid

Questions or comments?

call 516-341-0666, 8:30 am-4:30 pm ET, Monday-Friday

Drug Facts continued on back of label

TAMPER EVIDENT: DO NOT USE IF IMPRINTED SAFETY SEAL UNDER CAP IS BROKEN OR MISSING

Distributed by: Reliable-1 Laboratoreis LLC

Valley Stream, Ny 11580 www.reliable1labs.com

HOW SUPPLIED

Guaifenesin 400 mg

NDC: 71335-9616-1: 30 Tablets in a BOTTLE, PLASTIC

NDC: 71335-9616-2: 20 Tablets in a BOTTLE, PLASTIC

NDC: 71335-9616-3: 50 Tablets in a BOTTLE, PLASTIC

NDC: 71335-9616-4: 60 Tablets in a BOTTLE, PLASTIC

NDC: 71335-9616-5: 40 Tablets in a BOTTLE, PLASTIC

Store at 15°-30°C (59°-86°F)

Repackaged/Relabeled by:
Bryant Ranch Prepack, Inc.
Burbank, CA 91504

PACKAGE LABEL

Guaifenesin 400 mg Tablet